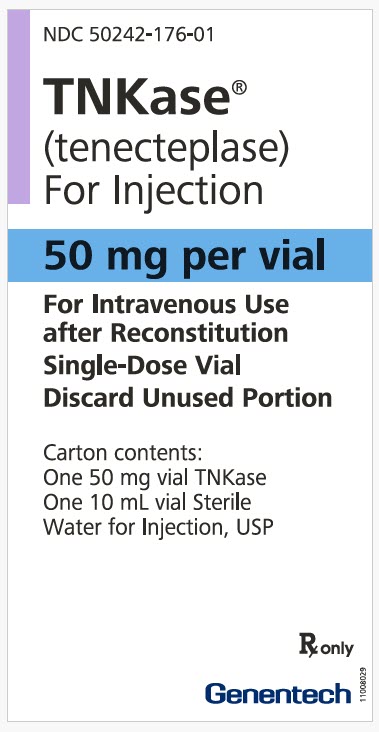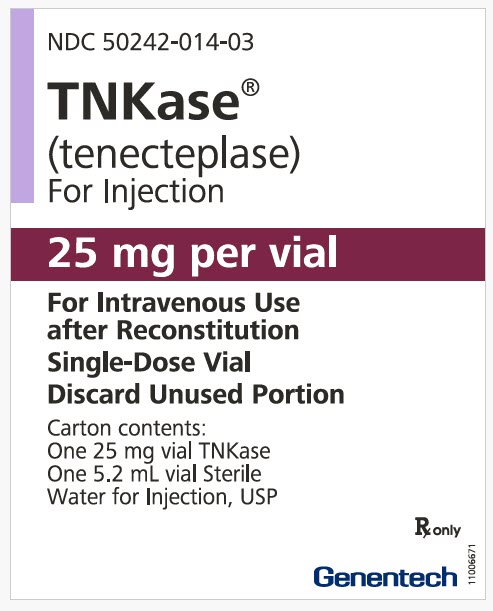 DRUG LABEL: TNKase
NDC: 50242-176 | Form: KIT | Route: INTRAVENOUS
Manufacturer: Genentech, Inc.
Category: prescription | Type: HUMAN PRESCRIPTION DRUG LABEL
Date: 20251215

ACTIVE INGREDIENTS: TENECTEPLASE 50 mg/10 mL
INACTIVE INGREDIENTS: ARGININE; PHOSPHORIC ACID; POLYSORBATE 20; WATER 10 mL/10 mL

HIGHLIGHTS OF PRESCRIBING INFORMATION

These highlights do not include all the information needed to use TNKASE safely and effectively. See full prescribing information for TNKASE.
TNKase® (tenecteplase) for injection, for intravenous use
Initial U.S. Approval: 2000

RECENT MAJOR CHANGES

Indications and Usage (1.1) | 02/2025
Dosage and Administration (2.1, 2.3) | 02/2025
Contraindications (4) | 02/2025
Warnings and Precautions (5.1) | 02/2025

1 INDICATIONS AND USAGE

TNKase is a tissue plasminogen activator (tPA) indicated:

- for the treatment of acute ischemic stroke (AIS) in adults. (1.1)
- to reduce the risk of death associated with acute ST elevation myocardial infarction (STEMI) in adults. (1.2)

2 DOSAGE AND ADMINISTRATION

- TNKase is for intravenous administration only, administered as a single bolus over 5 seconds. (2.1, 2.2)
- AIS
  - Initiate treatment as soon as possible and within 3 hours after the onset of stroke symptoms. (2.1)
  - Individualize dosage based on patient's weight; the maximum recommended dose is 25 mg (5 mL). (2.1)
- Acute STEMI
  - Initiate treatment as soon as possible after the onset of STEMI symptoms. (2.2)
  - Individualize dosage based on patient's weight; the maximum recommended dose is 50 mg (10 mL). (2.2)

3 DOSAGE FORMS AND STRENGTHS

For Injection: 25 mg or 50 mg lyophilized powder in a single-dose vial co-packaged with Sterile Water for Injection USP (diluent). (3)

4 CONTRAINDICATIONS

- AIS and STEMI
  - Active internal bleeding (4)
  - Intracranial or intraspinal surgery or trauma within 2 months (4)
  - Known bleeding diathesis (4)
  - Current severe uncontrolled hypertension (4)
  - Presence of intracranial conditions that may increase the risk of bleeding (e.g., intracranial neoplasm, arteriovenous malformation, or aneurysm) (4)
- AIS
  - Active intracranial hemorrhage (4)
- Acute STEMI
  - History of intracranial hemorrhage
  - History of ischemic stroke within 3 months (4)

5 WARNINGS AND PRECAUTIONS

- Bleeding: Increases the risk of bleeding. Avoid intramuscular injections. Monitor for bleeding. (5.1)
- Hypersensitivity: Monitor patients treated with TNKase during and for several hours after administration. If symptoms of hypersensitivity occur, initiate appropriate therapy (e.g., antihistamines, corticosteroids, epinephrine). (5.2)
- Thromboembolism: The use of thrombolytics can increase the risk of thrombo-embolic events in patients with high likelihood of left heart thrombus. (5.3)
- Cholesterol Embolization: Has been reported in patients treated with thrombolytic agents. (5.4)
- Arrhythmias: It is recommended that anti-arrhythmic therapy for bradycardia and/or ventricular irritability be available when TNKase is administered. (5.5)
- Increased Risk of Heart Failure and Recurrent Ischemia when used with Planned Percutaneous Coronary Intervention in STEMI: In patients with a large ST segment elevation myocardial infarction, choose either thrombolysis or PCI as the primary treatment for reperfusion. Rescue PCI or subsequent elective PCI may be performed after administration of thrombolytic therapies if medically appropriate. (5.6)

6 ADVERSE REACTIONS

The most common adverse reaction is bleeding. (6)

To report SUSPECTED ADVERSE REACTIONS, contact Genentech at 1-888-835-2555 or FDA at 1-800-FDA-1088 or www.fda.gov/medwatch.

7 DRUG INTERACTIONS

During TNKase therapy, results of coagulation tests and/or measures of fibrinolytic activity may be unreliable unless specific precautions are taken to prevent in vitro artifacts. (7.1)

FULL PRESCRIBING INFORMATION

1 INDICATIONS AND USAGE

1.1 Acute Ischemic Stroke

TNKase is indicated for the treatment of acute ischemic stroke (AIS) in adults.

1.2 Acute ST Elevation Myocardial Infarction

TNKase is indicated to reduce the risk of death associated with acute ST elevation myocardial infarction (STEMI) in adults.

2 DOSAGE AND ADMINISTRATION

2.1 Recommended Dosage for Acute Ischemic Stroke

Initiate treatment as soon as possible and within 3 hours after the onset of stroke symptoms.

TNKase is for intravenous (IV) administration only, administered as a single bolus over 5 seconds. Individualize dosage based on the patient's weight (see Table 1). The maximum recommended dose is 25 mg (5 mL).

Table 1 Recommended Dosage for Acute Ischemic Stroke
Patient Weight (kg) | TNKase (mg) | Volume TNKase to be administered (mL)
less than 60 kg | 15 mg | 3 mL
60 kg to less than 70 kg | 17.5 mg | 3.5 mL
70 kg to less than 80 kg | 20 mg | 4 mL
80 kg to less than 90 kg | 22.5 mg | 4.5 mL
90 kg or more | 25 mg | 5 mL

During and following TNKase administration for the treatment of acute ischemic stroke, frequently monitor and control blood pressure.

In patients without recent use of oral anticoagulants or heparin, TNKase treatment can be initiated prior to the availability of coagulation study results. If the pretreatment International Normalized Ratio (INR) is greater than 1.7 or the activated partial thromboplastin time (aPTT) is elevated, closely monitor patients [see Contraindications (4)].

2.2 Recommended Dosage for Acute ST Elevation Myocardial Infarction

Initiate treatment as soon as possible after the onset of STEMI symptoms.

TNKase is for intravenous (IV) administration only, administered as a single bolus over 5 seconds. Individualize dosage based on the patient's weight (see Table 2). The maximum recommended dose is 50 mg (10 mL).

Table 2 Recommended Dosage for Acute ST Elevation Myocardial Infarction
Patient Weight (kg) | TNKase (mg) | Volume TNKase to be administered (mL)
less than 60 kg | 30 mg | 6 mL
60 kg to less than 70 kg | 35 mg | 7 mL
70 kg to less than 80 kg | 40 mg | 8 mL
80 kg to less than 90 kg | 45 mg | 9 mL
90 kg or more | 50 mg | 10 mL

2.3 Preparation

Follow the steps below to prepare TNKase for administration:

- Only use the supplied Sterile Water for Injection diluent vial for reconstitution as shown below.

TNKase Vial Strength | Sterile Water for Injection Vial Volume
25 mg | 5.2 mL
50 mg | 10 mL

- Using a sterile syringe, aseptically withdraw the Sterile Water for Injection from the diluent vial and reconstitute the TNKase vial by directing the stream into the lyophilized powder to obtain a final concentration of 5 mg/mL. Slight foaming upon reconstitution is not unusual; any large bubbles will dissipate if the product is allowed to stand undisturbed for several minutes.
- Gently swirl until contents are completely dissolved. DO NOT SHAKE. The reconstituted preparation results in a colorless to pale yellow transparent solution.
- Determine the appropriate dose of TNKase [see Dosage and Administration (2.1, 2.2)] and withdraw the required volume (in milliliters) from the reconstituted vial into the syringe. Discard any unused solution.

2.4 Administration

Follow the steps below for administration of TNKase:

- Visually inspect the reconstituted product in the syringe for particulate matter and discoloration prior to administration.
- Precipitation may occur when TNKase is administered in an intravenous line containing dextrose. Flush dextrose-containing lines with 0.9% Sodium Chloride Injection solution prior to and following single bolus administration of TNKase.
- Using sterile technique, connect the syringe directly to the intravenous port.
- Administer reconstituted TNKase as a single intravenous bolus over 5 seconds.
- Because TNKase contains no antibacterial preservatives, reconstitute immediately before use. If the reconstituted TNKase is not used immediately, refrigerate the TNKase vial at 2°C to 8°C (36°F to 46°F) and use within 8 hours.
- Dispose of the syringe per established procedures.

2.5 Chemical Incompatibilities

TNKase is incompatible with dextrose containing solutions. When used together, precipitation may occur. Flush dextrose containing lines with 0.9% Sodium Chloride Injection solution before using TNKase.

3 DOSAGE FORMS AND STRENGTHS

For injection: 25 mg or 50 mg as a white to pale yellow lyophilized powder in a single-dose vial for reconstitution with co-packaged Sterile Water for Injection, USP (diluent).

4 CONTRAINDICATIONS

AIS and Acute STEMI

TNKase is contraindicated in any patients with:

- Active internal bleeding
- Intracranial or intraspinal surgery or trauma within 2 months
- Known bleeding diathesis
- Current severe uncontrolled hypertension
- Presence of intracranial conditions that may increase the risk of bleeding (e.g., intracranial neoplasm, arteriovenous malformation, or aneurysm)

AIS

TNKase is also contraindicated in patients for the treatment of AIS with:

- Active intracranial hemorrhage

Acute STEMI

TNKase is also contraindicated in patients for the treatment of STEMI with:

- History of intracranial hemorrhage
- History of ischemic stroke within 3 months

5 WARNINGS AND PRECAUTIONS

5.1 Bleeding

TNKase can cause significant, sometimes fatal, internal or external bleeding, especially at arterial and venous puncture sites. Concomitant use of other drugs that impair hemostasis increases the risk of bleeding. Avoid intramuscular injections and trauma to the patient while on TNKase. Perform arterial and venous punctures carefully and only as required. To minimize bleeding from noncompressible sites, avoid internal jugular and subclavian venous punctures. If an arterial puncture is necessary during TNKase administration, use an upper extremity vessel that is accessible to manual compression, apply pressure for at least 30 minutes, and monitor the puncture site closely.

Should serious bleeding that is not controlled by local pressure occur, discontinue any concomitant heparin or antiplatelet agents immediately and treat appropriately. Because of the higher risk of intracranial hemorrhage in patients treated for acute ischemic stroke, limit treatment to facilities that can provide timely access to appropriate evaluation and management of intracranial hemorrhage.

Aspirin and heparin have been administered concomitantly with and following administration of TNKase in the management of acute myocardial infarction, but the concomitant administration of heparin and aspirin with and following administration of TNKase for the treatment of acute ischemic stroke during the first 24 hours after symptom onset has not been investigated. Because heparin, aspirin, or TNKase may cause bleeding complications, carefully monitor for bleeding, especially at arterial puncture sites. Hemorrhage can occur 1 or more days after administration of TNKase, while patients are still receiving anticoagulant therapy.

If serious bleeding occurs, treat appropriately. In the following conditions, the risks of bleeding with TNKase therapy for all approved indications are increased and should be weighed against the anticipated benefits:

- Recent major surgery or procedure (e.g., coronary artery bypass graft, obstetrical delivery, organ biopsy, previous puncture of noncompressible vessels)
- Cerebrovascular disease
- Recent intracranial hemorrhage (if not contraindicated)
- Recent gastrointestinal or genitourinary bleeding
- Recent trauma
- Hypertension: systolic BP above 175 mm Hg or diastolic BP above 110 mm Hg
- Acute pericarditis
- Subacute bacterial endocarditis
- Hemostatic defects including those secondary to severe hepatic or renal disease
- Significant hepatic dysfunction
- Pregnancy
- Diabetic hemorrhagic retinopathy, or other hemorrhagic ophthalmic conditions
- Septic thrombophlebitis or occluded AV cannula at seriously infected site
- Advanced age [see Use in Specific Populations (8.5)]
- Patients currently receiving anticoagulants (e.g., warfarin sodium)

Any other condition in which bleeding constitutes a significant hazard or would be particularly difficult to manage because of its location.

5.2 Hypersensitivity

Hypersensitivity, including urticarial / anaphylactic reactions, have been reported after administration of TNKase (e.g., anaphylaxis, angioedema, laryngeal edema, rash, and urticaria). Monitor patients treated with TNKase during and for several hours after administration. If symptoms of hypersensitivity occur, initiate appropriate therapy (e.g., antihistamines, corticosteroids, epinephrine).

5.3 Thromboembolism

The use of thrombolytics can increase the risk of thrombo-embolic events in patients with high likelihood of left heart thrombus, such as patients with mitral stenosis or atrial fibrillation.

5.4 Cholesterol Embolization

Cholesterol embolism has been reported in patients treated with thrombolytic agents. Investigate cause of any new embolic event and treat appropriately.

5.5 Arrhythmias

Coronary thrombolysis may result in arrhythmias associated with reperfusion. These arrhythmias (such as sinus bradycardia, accelerated idioventricular rhythm, ventricular premature depolarizations, ventricular tachycardia) may be managed with standard anti-arrhythmic measures. It is recommended that anti-arrhythmic therapy for bradycardia and/or ventricular irritability be available when TNKase is administered.

5.6 Increased Risk of Heart Failure and Recurrent Ischemia when used with Planned Percutaneous Coronary Intervention (PCI) in STEMI

In a trial of patients with STEMI, there were worse outcomes in the individual components of the primary endpoint between TNKase plus PCI versus PCI alone (mortality 6.7% vs. 4.9%, respectively; cardiogenic shock 6.3% vs. 4.8%, respectively; and CHF 12% vs. 9.2%, respectively). In addition, there were worse outcomes in recurrent MI (6.1% vs. 3.7%, respectively; p = 0.03) and repeat target vessel revascularization (6.6% vs. 3.4%, respectively; p = 0.0045) in patients receiving TNKase plus PCI versus PCI alone [see Clinical Studies (14.2)]. In patients with large ST segment elevation myocardial infarction, physicians should choose either thrombolysis or PCI as the primary treatment strategy for reperfusion. Rescue PCI or subsequent elective PCI may be performed after administration of thrombolytic therapies if medically appropriate; however, the optimal use of adjunctive antithrombotic and antiplatelet therapies in this setting is unknown.

6 ADVERSE REACTIONS

The following clinically significant adverse reactions are discussed in other sections of the label:

- Bleeding [see Contraindications (4), Warnings and Precautions (5.1)]
- Hypersensitivity [see Warnings and Precautions (5.2)]
- Thromboembolism [see Warnings and Precautions (5.3)]
- Cholesterol Embolization [see Warnings and Precautions (5.4)]
- Arrhythmias [see Warnings and Precautions (5.5)]
- Increased Risk of Heart Failure and Recurrent Ischemia when used with Planned Percutaneous Coronary Intervention (PCI) in STEMI [see Warnings and Precautions (5.6)]

6.1 Clinical Trials Experience

Because clinical trials are conducted under widely varying conditions, adverse reaction rates observed in the clinical trials of a drug cannot be directly compared to rates in the clinical trials of another drug and may not reflect the rates observed in practice.

The most frequent adverse reaction associated with TNKase in all approved indications is bleeding.

Acute Ischemic Stroke

In Trial 1, the safety of TNKase for the treatment of acute ischemic stroke (AIS) was evaluated in 592 patients who received TNKase at the recommended dosage within 0 to 3 hours of the onset of stroke symptoms (Alteplase compared to Tenecteplase (AcT); Trial 1) [see Dosage and Administration (2.1) and Clinical Studies (14.1)].

Table 3 describes the incidence of adverse reactions in patients with AIS in Trial 1.

Table 3 Incidence of Adverse Reactions in Trial 1 in Patients Treated for Acute Ischemic Stroke Within 0 to 3 Hours from Symptom Onset
Adverse Reaction | TNKase N=592 % | Activase N= 555 %
Death | 15.0 | 15.0
Symptomatic intracerebral hemorrhage [intracerebral hemorrhage that, in the opinion of the investigator, was temporally related to and directly responsible for worsening of the neurological condition] | 3.4 | 3.1
Extracranial (peripheral) bleeding requiring blood transfusion | 1.0 | 0.7
Orolingual angioedema | 1.0 | 1.4

7 DRUG INTERACTIONS

7.1 Drug/Laboratory Test Interactions

During TNKase therapy, results of coagulation tests and/or measures of fibrinolytic activity may be unreliable unless specific precautions are taken to prevent in vitro artifacts. Tenecteplase is an enzyme that, when present in blood in pharmacologic concentrations, remains active under in vitro conditions. This can lead to degradation of fibrinogen in blood samples removed for analysis.

8 USE IN SPECIFIC POPULATIONS

8.1 Pregnancy

Risk Summary

There are risks to the mother and fetus from acute ST elevation myocardial infarction and acute ischemic stroke, which are medical emergencies in pregnancy and can be fatal if left untreated (see Clinical Considerations). Published data consisting of a small number of case reports involving the use of related thrombolytic agents in pregnant women have not identified an increased risk of major birth defects. There are no data on the use of tenecteplase during pregnancy to evaluate for a drug-associated risk of major birth defects, miscarriage, or adverse maternal or fetal outcomes.

TNKase does not elicit maternal and direct embryo toxicity in rabbits following a single IV administration. In developmental toxicity studies conducted in rabbits, the no observable effect level (NOEL) of a single IV administration of TNKase on maternal or developmental toxicity (5 mg/kg) was approximately 7 times human exposure (based on AUC) at the dose for STEMI.

The estimated background risk of major birth defects and miscarriage for the indicated population is unknown. All pregnancies have a background risk of birth defect, loss, or other adverse outcomes. In the U.S. general population, the estimated background risk of major birth defects and miscarriage in clinically recognized pregnancies is 2% to 4% and 15% to 20%, respectively.

Clinical Considerations

Disease-Associated Maternal and/or Embryo/Fetal Risk

Acute ST elevation myocardial infarction and acute ischemic stroke are medical emergencies which can be fatal if left untreated. Life-sustaining therapy for the pregnant woman should not be withheld because of potential concerns regarding the effects of tenecteplase on the fetus.

8.2 Lactation

Risk Summary

There are no data on the presence of tenecteplase in either human or animal milk, the effects on the breastfed infant, or the effect on milk production. The developmental and health benefits of breastfeeding should be considered along with the mother's clinical need for TNKase and any potential adverse effects on the breastfed infant from the TNKase or from the underlying maternal condition.

8.4 Pediatric Use

The safety and effectiveness of TNKase in pediatric patients have not been established.

8.5 Geriatric Use

Of the total number of TNKase-treated patients within 0-3 hours in Trial 1 for acute ischemic stroke (AIS), 426 (72%) were 65 years of age and older, and 290 (49%) were 75 years of age and older [see Clinical Studies (14.1)]. No overall differences in safety were observed between patients over 65 years old with AIS and younger patients, but greater sensitivity of some older individuals cannot be ruled out.

In the ASSENT-2 study, 41% (3500/8458) of STEMI patients who were treated with TNKase were aged 65 years or older. In this population, rates of 30-day mortality, stroke, intracranial hemorrhage and major bleeds requiring blood transfusion or leading to hemodynamic complications were higher than in those aged less than 65 years.

11 DESCRIPTION

Tenecteplase is a tissue plasminogen activator (tPA) produced by recombinant DNA technology using a mammalian cell line (Chinese Hamster Ovary cells). Tenecteplase is a 527-amino acid glycoprotein developed by introducing the following modifications to the complementary DNA (cDNA) for natural human tPA: a substitution of threonine 103 with asparagine, and a substitution of asparagine 117 with glutamine, both within the kringle 1 domain, and a tetra-alanine substitution at amino acids 296–299 in the protease domain. It has a molecular weight of 58,742 daltons. Biological potency is determined by an in vitro clot lysis assay and is expressed in tenecteplase specific units. The specific activity of tenecteplase has been defined as 200 units/mg.

TNKase (tenecteplase) for injection is a sterile, white to pale yellow, lyophilized powder for intravenous bolus administration after reconstitution with Sterile Water for Injection, USP.

Each 25 mg single-dose vial of TNKase nominally contains 25 mg of tenecteplase, arginine (261 mg), phosphoric acid (approximately 80 mg), and polysorbate 20 (2.0 mg). Following reconstitution with the supplied 5.2 mL single-dose vial of Sterile Water for Injection, USP, the final concentration is 5 mg/mL with a pH of approximately 7.3.

Each 50 mg single-dose vial of TNKase nominally contains 50 mg of tenecteplase, arginine (522 mg), phosphoric acid (approximately 160 mg), and polysorbate 20 (4.0 mg). Following reconstitution with the supplied 10 mL single-dose vial of Sterile Water for Injection, USP, the final concentration is 5 mg/mL with a pH of approximately 7.3.

12 CLINICAL PHARMACOLOGY

12.1 Mechanism of Action

Tenecteplase is a modified form of human tissue plasminogen activator (tPA) that binds to fibrin and converts plasminogen to plasmin. In the presence of fibrin, in vitro studies demonstrate that tenecteplase-mediated conversion of plasminogen to plasmin is increased relative to its conversion in the absence of fibrin. This fibrin specificity decreases systemic activation of plasminogen and the resulting degradation of circulating fibrinogen as compared to a molecule lacking this property. The clinical significance of fibrin-specificity on safety (e.g., bleeding) or efficacy has not been established.

12.2 Pharmacodynamics

Following administration of 30, 40, or 50 mg of TNKase in patients with STEMI, there are decreases in circulating fibrinogen (4%–15%) and plasminogen (11%–24%).

12.3 Pharmacokinetics

Distribution

In patients with STEMI, TNKase administered as a single IV bolus exhibits a biphasic disposition from the plasma.

Volume of distribution at central compartment ranges from 4.22 to 5.43 L, approximating plasma volume. Steady-state volume of distribution was approximately 50% greater (6.12 to 8.01 L), suggestive of some extravascular distribution.

Elimination

After IV bolus administration in patients with STEMI, the terminal phase half-life of tenecteplase was 90 to 130 minutes. In 99 of 104 patients treated with TNKase, TNKase has linear PK with mean maximum concentrations increased in a dose-proportional manner and mean plasma clearance was similar for the 30, 40, and 50 mg doses ranging from 99 to 119 mL/min.

Metabolism

Liver metabolism is the major clearance mechanism for tenecteplase.

Body weight

A stepwise linear regression analysis indicated that total body weight explained 19% of the variability in plasma clearance and 11% of the variability in volume of distribution in patients with STEMI.

12.6 Immunogenicity

The observed incidence of anti-drug antibodies is highly dependent on the sensitivity and specificity of the assay. Differences in assay methods preclude meaningful comparisons of the incidence of anti-drug antibodies in the studies described below with the incidence of anti-drug antibodies in other studies, including those of tenecteplase or of other tenecteplase products.

In a study of subjects with STEMI, four of 625 (0.64%) STEMI patients tested for antibody formation to TNKase had a positive antibody titer at 30 days in studies with TNKase.

13 NONCLINICAL TOXICOLOGY

13.1 Carcinogenesis, Mutagenesis, Impairment of Fertility

Studies in animals have not been performed to evaluate the carcinogenic potential, mutagenicity, or the effect on fertility.

14 CLINICAL STUDIES

14.1 Acute Ischemic Stroke

The Alteplase compared to Tenecteplase (AcT) trial (NCT03889249, Trial 1) was a registry-linked, multicenter, parallel group, open-label, randomized trial with blinded outcome assessment that investigated the non-inferiority of TNKase (tenecteplase) compared to Activase (alteplase) in treating patients with acute ischemic stroke (AIS) that presented with a disabling neurologic deficit. Endovascular thrombectomy was allowed if patients were eligible based on standard of care.

A total of 1147 patients were treated within 3 hours of symptom onset and were included in the intent to treat (ITT) population. In the ITT population, the mean age was 72 years, 53% of patients were male, 24% were White, 5% were Asian, and 70% did not have a race reported or their race was unknown. Among the ITT population, the median baseline National Institute of Health Stroke Scale (NIHSS) score was 10, 27% of patients had a large vessel occlusion on baseline CT angiography, and the median stroke symptom onset to thrombolysis time was 108 minutes. Demographics and other baseline characteristics were generally balanced between the treatment groups.

Patients were randomized (1:1) to receive a single IV bolus of TNKase or a one-hour infusion of 0.9 mg/kg Activase (10% administered as an IV bolus over 1 minute and the remaining 90% given as an infusion over 1 hour; maximum dose 90 mg). TNKase was dosed using actual or estimated weight in a body weight-tiered fashion at the recommended dosage [see Dosage and Administration (2.1)]. Administration of antiplatelet agents or other antithrombotic products were prohibited within the first 24 hours after administration of TNKase or Activase.

In Trial 1, efficacy was assessed as a pre-defined favorable clinical outcome based on the proportion of patients that were treated within 3 hours of symptom onset who achieved a modified Rankin Scale (mRS) score of 0–1 at 90–120 days, as assessed by the Rankin Focused Assessment. The mRS is a 7-point scale which captures disability after stroke; higher scores indicate an increased amount of disability. A score of 0 represents no symptoms or disability, where a score of 6 represents death. A score of 0 or 1 represents a favorable clinical outcome. The results comparing TNKase with Activase in patients treated within 3 hours of symptom onset are presented in Table 4. Study results demonstrated no significant differences between treatment groups. Although the trial enrolled patients who were treated within 0-4.5 hours of stroke symptom onset, the subset of patients treated within 0-3 hours was used to assess efficacy of TNKase because the comparator, Activase, is approved for use within 0-3 hours of stroke symptom onset.

Table 4 Trial 1: Efficacy Outcome Results in Patients with Acute Ischemic Stroke Treated Within 0-3 Hours of Symptom Onset (ITT Population)
Endpoint | TNKase N = 592 | Activase N = 555
Proportion of Patients with mRS 0-1 at 90-120 days | 36.6% | 35.9%
Unadjusted Risk Difference % (95% CI) | 0.7% (-4.9%, 6.3%)
CI: Confidence Interval
mRS: Modified Rankin Score

A similar treatment effect in achieving a mRS score 0–1 was observed in exploratory subgroups defined by age, gender, and baseline NIHSS score.

14.2 Acute ST Elevation Myocardial Infarction

ASSENT-2

The Assessment of the Safety and Efficacy of a New Thrombolytic (ASSENT-2) study was an international, randomized, double-blind trial that compared 30-day mortality rates in 16,949 patients assigned to receive an IV bolus dose of TNKase or an accelerated infusion of Activase (alteplase). Eligibility criteria included onset of chest pain within 6 hours of randomization and ST-segment elevation or left bundle branch block on electrocardiogram (ECG). Patients were to be excluded from the trial if they received GP IIb/IIIa inhibitors within the previous 12 hours. TNKase was dosed using actual or estimated weight in a weight-tiered fashion as described in Dosage and Administration (2.2). All patients were to receive 150–325 mg of aspirin administered as soon as possible, followed by 150–325 mg daily. Intravenous heparin was to be administered as soon as possible: for patients weighing ≤ 67 kg, heparin was administered as a 4000-unit IV bolus followed by infusion at 800 U/hr; for patients weighing > 67 kg, heparin was administered as a 5000-unit IV bolus followed by infusion at 1000 U/hr. Heparin was continued for 48 to 72 hours with infusion adjusted to maintain aPTT at 50–75 seconds. The use of GP IIb/IIIa inhibitors was discouraged for the first 24 hours following randomization. The results of the primary endpoint (30-day mortality rates with non-parametric adjustment for the covariates of age, Killip class, heart rate, systolic blood pressure and infarct location) along with selected other 30-day endpoints are shown in Table 5.

Table 5 ASSENT-2 Mortality, Stroke, and Combined Outcome of Death or Stroke Measured at Thirty Days
30-Day Events | TNKase (n = 8461) | Accelerated Activase (n = 8488) | Relative Risk TNKase/Activase (95% CI)
Mortality | 6.2% | 6.2% | 1.00 (0.89, 1.12)
Intracranial Hemorrhage (ICH) | 0.9% | 0.9% | 0.99 (0.73, 1.35)
Any Stroke | 1.8% | 1.7% | 1.07 (0.86, 1.35)
Death or Nonfatal Stroke | 7.1% | 7.0% | 1.01 (0.91, 1.13)

Rates of mortality and the combined endpoint of death or stroke among pre-specified subgroups, including age, gender, time to treatment, infarct location, and history of previous myocardial infarction, demonstrate consistent relative risks across these subgroups. There was insufficient enrollment of non-Caucasian patients to draw any conclusions regarding relative efficacy in racial subsets.

Rates of in-hospital procedures, including percutaneous transluminal coronary angioplasty (PTCA), stent placement, intra-aortic balloon pump (IABP) use, and coronary artery bypass graft (CABG) surgery, were similar between the TNKase and Activase groups.

TIMI-10B

TIMI 10B was an open-label, controlled, randomized, dose-ranging, angiography study which utilized a blinded core laboratory for review of coronary arteriograms. Patients (n = 837) presenting within 12 hours of symptom onset were treated with fixed doses of 30, 40, or 50 mg of TNKase or the accelerated infusion of Activase and underwent coronary arteriography at 90 minutes. The primary endpoint was the rate of TIMI Grade 3 flow at 90 minutes. The results showed that the 40 mg and 50 mg doses were similar to accelerated infusion of Activase in restoring patency. TIMI Grade 3 flow and TIMI Grade 2/3 flow at 90 minutes are shown in Table 6. The exact relationship between coronary artery patency and clinical activity has not been established.

Table 6 TIMI 10B Patency Rates TIMI Grade Flow at 90 Minutes
 | Activase ≤100 mg (n=311) | TNKase 30 mg (n=302) | TNKase 40 mg (n=148) | TNKase 50 mg (n=76)
TIMI Grade 3 Flow (95% CI) | 62.7% (57.1%, 68.1%) | 54.3% (48.5%, 60.0%) | 62.8% (54.5%, 70.6%) | 65.8% (54.0%, 76.3%)
TIMI Grade 2/3 Flow (95% CI) | 81.7% (76.9%, 85.8%) | 76.8% (71.6%, 81.5%) | 79.1% (71.6%, 85.3%) | 88.2% (78.7%, 94.4%)

The angiographic results from TIMI 10B and the safety data from ASSENT-1, an additional uncontrolled safety study of 3,235 TNKase-treated patients, provided the framework to develop a weight-tiered TNKase dose regimen. Exploratory analyses suggested that a weight-adjusted dose of 0.5 to 0.6 mg/kg of TNKase resulted in a better patency to bleeding relationship than fixed doses of TNKase across a broad range of patient weights.

ASSENT-4 PCI

The Assessment of the Safety and Efficacy of a New Treatment Strategy with Percutaneous Coronary Intervention (ASSENT-4 PCI) was a phase IIIb/IV study designed to assess the safety and effectiveness of a strategy of administering full dose TNKase with a single bolus of 4000 U of unfractionated heparin in patients with STEMI, in whom primary percutaneous coronary intervention (PCI) was planned, but in whom a delay of 1-3 hours was anticipated before PCI. The trial was prematurely terminated with 1667 randomized patients (75 of whom were in the United States) due to a numerically higher mortality in the patients receiving TNKase prior to primary PCI versus PCI without TNKase (median time from randomization to balloon was 115 minutes in patients who were treated with TNKase plus PCI versus 107 minutes in patients who were treated with PCI alone). The incidence of the 90-day primary endpoint, a composite of death or cardiogenic shock or congestive heart failure (CHF) within 90 days, was 18.6% in patients treated with TNKase plus PCI versus 13.4% in those treated with PCI alone (p = 0.0045; RR 1.39 (95% CI 1.11-1.74)).

There were worse outcomes in the individual components of the primary endpoint between TNKase plus PCI versus PCI alone (mortality 6.7% vs. 4.9%, respectively; cardiogenic shock 6.3% vs. 4.8%, respectively; and CHF 12.0% vs. 9.2%, respectively). In addition, there were worse outcomes in recurrent MI (6.1% vs. 3.7%, respectively; p = 0.03) and repeat target vessel revascularization (6.6% vs. 3.4%, respectively; p = 0.004) in patients receiving TNKase plus PCI versus PCI alone [see Warnings and Precautions (5.6)].

There was no difference in in-hospital major bleeding between the two groups (5.6% vs. 4.4% for TNKase plus PCI vs. PCI alone, respectively). For patients treated with TNKase plus PCI, in-hospital rates of intracranial hemorrhage and total stroke were similar to those observed in previous trials (0.97% and 1.8%, respectively); however, none of the patients treated with PCI alone experienced a stroke (ischemic, hemorrhagic or other).

16 HOW SUPPLIED/STORAGE AND HANDLING

16.1 How Supplied

TNKase (tenecteplase) for injection is supplied as a sterile, white to pale yellow lyophilized powder in single-dose vials under partial vacuum, co-packaged with a single-dose vial of Sterile Water for Injection, USP, for reconstitution, as follows:

TNKase Strength | Sterile Water for Injection Volume | NDC
25 mg | 5.2 mL | 50242-014-03
50 mg | 10 mL | 50242-176-01

16.2 Storage and Handling

Store lyophilized TNKase at room temperature up to 30°C (86°F) or refrigerated at 2°C to 8°C (36°F to 46°F). Do not use beyond the expiration date stamped on the vial.

For storage information for reconstituted TNKase, see Dosage and Administration (2.4).

17 PATIENT COUNSELING INFORMATION

Bleeding

Inform patients that bleeding can occur 1 or more days after administration of TNKase [see Warnings and Precautions (5.1)]. Instruct patients to contact a healthcare provider if they experience signs or symptoms consistent with bleeding (e.g., unusual bruising; pink or brown urine; red, black, or tarry stools; coughing up blood; vomiting blood or blood that looks like coffee grounds) or symptoms of a stroke.

TNKase® (tenecteplase)

Manufactured by:
Genentech, Inc.

A Member of the Roche Group
1 DNA Way
South San Francisco, CA 94080-4990

U.S. License No. 1048

TNKase® is a registered trademark of Genentech, Inc.
©2025 Genentech, Inc.

PRINCIPAL DISPLAY PANEL - Kit Carton - 50 mg

NDC 50242-176-01

TNKase®
(tenecteplase)
For Injection

50 mg per vial

For Intravenous Use
after Reconstitution
Single-Dose Vial
Discard Unused Portion

Carton contents:
One 50 mg vial TNKase
One 10 mL vial Sterile
Water for Injection, USP

Rx only

Genentech

11008029

PRINCIPAL DISPLAY PANEL - Kit Carton - 25 mg

NDC 50242-014-03

TNKase®
(tenecteplase)
For Injection

25 mg per vial

For Intravenous Use
after Reconstitution
Single-Dose Vial
Discard Unused Portion

Carton contents:
One 25 mg vial TNKase
One 5.2 mL vial Sterile
Water for Injection, USP

Rx only

Genentech

11006671